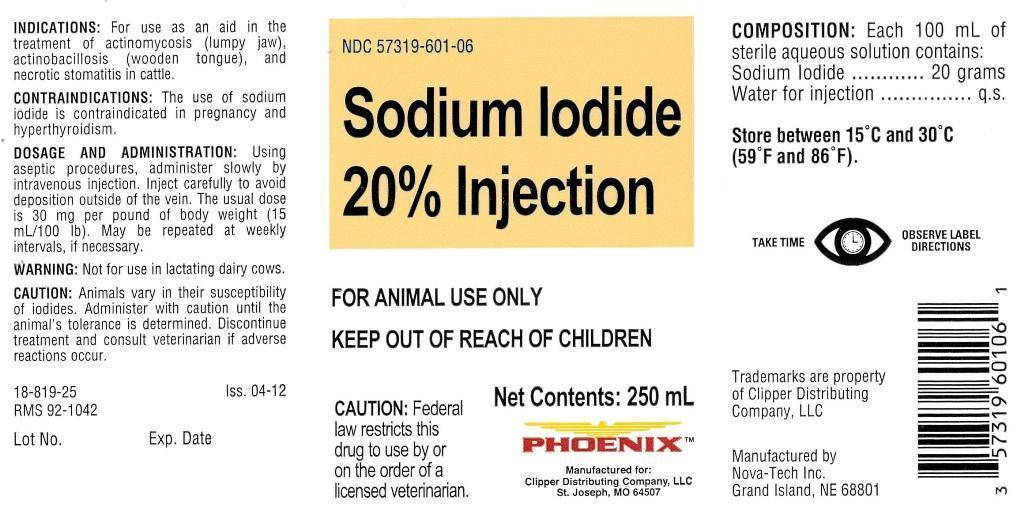 DRUG LABEL: Sodium Iodide 20%
NDC: 57319-601 | Form: INJECTION, SOLUTION
Manufacturer: Clipper
Category: animal | Type: PRESCRIPTION ANIMAL DRUG LABEL
Date: 20140512

ACTIVE INGREDIENTS: SODIUM IODIDE 20 g/250 mL

Sodium Iodide 20% Injection

INDICATIONS:

For use as an aid in the treatment of actinomycosis (lumpy jaw), actinobacillosis (wooden tongue), and necrotic stomatitis in cattle.

CONTRAINDICATIONS:

The use of sodium iodide is contraindicated in pregnancy and hyperthyroidism.

DOSAGE AND ADMINISTRATION:

Using aseptic procedures, administer slowly by intravenous injection. Inject carefully to avoid deposition outside of the vein. The usual dose is 30 mg per pound of body weight (15 mL/100 lb). May be repeated at weekly intervals, if necessary.

WARNING:

Not for use in lactating dairy cows.

CAUTION:

Animals vary in their susceptibility of iodides. Administer with caution until the animal's tolerance is determined. Discontinue treatment and consult veterinarian if adverse reactions occur.

INFORMATION FOR OWNERS/CAREGIVERS

18-819-25

Iss. 04-12

RMS 92-1042

Lot No.

Exp. Date

VETERINARY INDICATIONS

FOR ANIMAL USE ONLY

KEEP OUT OF REACH OF CHILDREN

CAUTION:

Federal law restricts this drug to use by or on the order of a licensed veterinarian.

COMPOSITION:

Each 100 mL of sterile aqueous solution contains:

Sodium Iodide................20 grams

Water for injection...................q.s.

STORAGE AND HANDLING

Store between 15 degrees C and 30 degrees C (59 degrees F and 86 degrees F).

WARNINGS

TAKE TIME OBSERVE LABEL DIRECTIONS

INFORMATION FOR OWNERS/CAREGIVERS

Trademarks are property of Clipper Distributing Company, LLC

Manufactured by Nova-Tech Inc. Grand Island, NE 68801

Net Contents: 250 mL